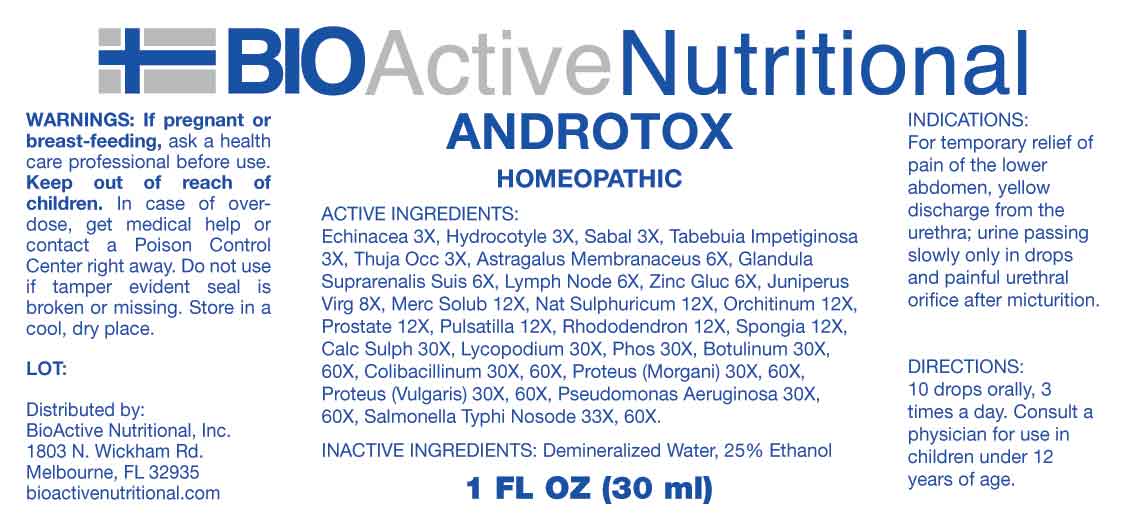 DRUG LABEL: Androtox
NDC: 43857-0523 | Form: LIQUID
Manufacturer: BioActive Nutritional, Inc.
Category: homeopathic | Type: HUMAN OTC DRUG LABEL
Date: 20230803

ACTIVE INGREDIENTS: ECHINACEA ANGUSTIFOLIA WHOLE 3 [hp_X]/1 mL; CENTELLA ASIATICA WHOLE 3 [hp_X]/1 mL; SAW PALMETTO 3 [hp_X]/1 mL; TABEBUIA IMPETIGINOSA BARK 3 [hp_X]/1 mL; THUJA OCCIDENTALIS LEAFY TWIG 3 [hp_X]/1 mL; ASTRAGALUS PROPINQUUS ROOT 6 [hp_X]/1 mL; SUS SCROFA ADRENAL GLAND 6 [hp_X]/1 mL; SUS SCROFA LYMPH 6 [hp_X]/1 mL; ZINC GLUCONATE 6 [hp_X]/1 mL; JUNIPERUS VIRGINIANA TWIG 8 [hp_X]/1 mL; MERCURIUS SOLUBILIS 12 [hp_X]/1 mL; SODIUM SULFATE 12 [hp_X]/1 mL; SUS SCROFA TESTICLE 12 [hp_X]/1 mL; SUS SCROFA PROSTATE 12 [hp_X]/1 mL; PULSATILLA PRATENSIS WHOLE 12 [hp_X]/1 mL; RHODODENDRON AUREUM LEAF 12 [hp_X]/1 mL; SPONGIA OFFICINALIS SKELETON, ROASTED 12 [hp_X]/1 mL; CALCIUM SULFATE ANHYDROUS 30 [hp_X]/1 mL; LYCOPODIUM CLAVATUM SPORE 30 [hp_X]/1 mL; PHOSPHORUS 30 [hp_X]/1 mL; BOTULINUM TOXIN TYPE A 30 [hp_X]/1 mL; ESCHERICHIA COLI 30 [hp_X]/1 mL; PROTEUS VULGARIS 30 [hp_X]/1 mL; PSEUDOMONAS AERUGINOSA 30 [hp_X]/1 mL; PROTEUS MORGANII 30 [hp_X]/1 mL; SALMONELLA ENTERICA SUBSP. ENTERICA SEROVAR TYPHI 33 [hp_X]/1 mL
INACTIVE INGREDIENTS: WATER; ALCOHOL

DRUG FACTS:

ACTIVE INGREDIENTS:

Echinacea 3X, Hydrocotyle Asiatica 3X, Sabal Serrulata 3X, Tabebuia Impetiginosa 3X, Thuja Occidentalis 3X, Astragalus Membranaceus 6X, Glandula Suprarenalis Suis 6X, Lymph Node 6X, Zincum Gluconicum 6X, Juniperus Virginiana 8X, Mercurius Solubilis 12X, Natrum Sulphuricum 12X, Orchitinum 12X, Prostate 12X, Pulsatilla 12X, Rhododendron Chrysanthum 12X, Spongia Tosta 12X, Calcarea Sulphurica 30X, Lycopodium Clavatum 30X, Phosphorus 30X, Botulinum 30X, 60X, Colibacillinum Cum Natrum Muriaticum 30X, 60X, Proteus (Morgani) 30X, 60X, Proteus (Vulgaris) 30x, 60X, Pseudomonas Aeruginosa 30X, 60X, Salmonella Typhi Nosode 33X, 60X.

INDICATIONS:

For temporary relief of pain of the lower abdomen, yellow discharge from the urethra; urine passing slowly only in drops and painful urethral orifice after micturition.

WARNINGS:

If pregnant or breast-feeding, ask a health care professional before use.

Keep out of reach of children. In case of overdose, get medical help or contact a Poison Control Center right away.

Do not use if tamper evident seal is broken or missing.

Store in cool, dry place.

KEEP OUT OF REACH OF CHILDREN:

In case of overdose, get medical help or contact a Poison Control Center right away.

DIRECTIONS:

10 drops orally, 3 times a day. Consult a physician for use in children under 12 years of age.

INDICATIONS:

For temporary relief of pain of the lower abdomen, yellow discharge from the urethra; urine passing slowly only in drops and painful urethral orifice after micturition.

INACTIVE INGREDIENTS:

Demineralized Water, 25% Ethanol

QUESTIONS:

Distributed by:
BioActive Nutritional, Inc.
1803 N. Wickham Rd.
Melbourne, FL 32935
bioactivenutritional.com

PACKAGE LABEL DISPLAY:

BIOActive Nutritional

ANDROTOX

HOMEOPATHIC

1 FL OZ (30 ml)